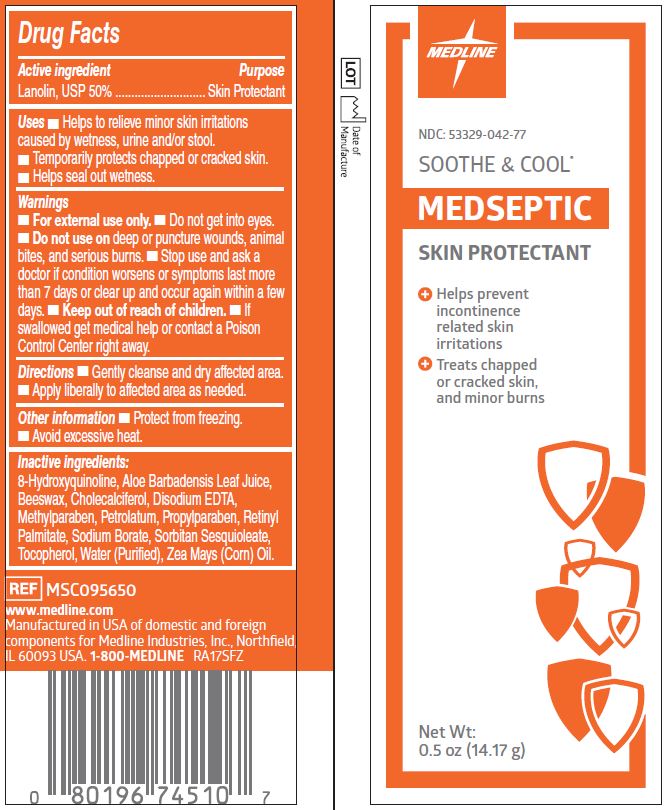 DRUG LABEL: Soothe and Cool Free Medseptic
NDC: 53329-042 | Form: OINTMENT
Manufacturer: Medline Industries, LP
Category: otc | Type: HUMAN OTC DRUG LABEL
Date: 20241126

ACTIVE INGREDIENTS: LANOLIN 500 mg/1 g
INACTIVE INGREDIENTS: ALOE VERA LEAF; YELLOW WAX; CHOLECALCIFEROL; EDETATE DISODIUM; METHYLPARABEN; OXYQUINOLINE; PETROLATUM; PROPYLPARABEN; VITAMIN A PALMITATE; SODIUM BORATE; WATER; CORN OIL

042 Soothe & Cool Medseptic Skin Protectant

Active ingredient

Lanolin, USP 50%

Purpose

Skin protectant

Uses

- helps to relieve minor skin irritations caused by wetness, urine and/or stool
- temporarily protects chapped or cracked skin.
- helps seal out wetness

Warnings

For external use only

When using this product

- do not get into eyes
- do not use on deep or puncture wounds, animal bites, and serious burns

Stop use and ask a doctor if

- condition worsens or symptoms persist for more than 7 days, or clear upand occur again within a few days

Keep out of reach of children.

If swallowed, get medical help or contact a Poison Control right away.

Directions

- gently cleanse and dry affected area
- apply liberally to affected area as needed.

Inactive ingredients

8-hydroxyquinoline, aloe barbadensis leaf juice, beeswax, cholecalciferol, disodium EDTA, methylparaben, petrolatum, propylparaben, retinyl palmitate, sodium borate, sorbitan sesquioleate, tocopherol, water, zea mays (corn) oil

Manufacturing Information

Manufactured for: Medline Industries, Inc.

Three Lakes Drive, Northfield, IL 60093 USA

Manufactured in USA of domestic and foreign components

www.medline.com

1-800-MEDLINE

REF: MSC095650

RA17SFZ